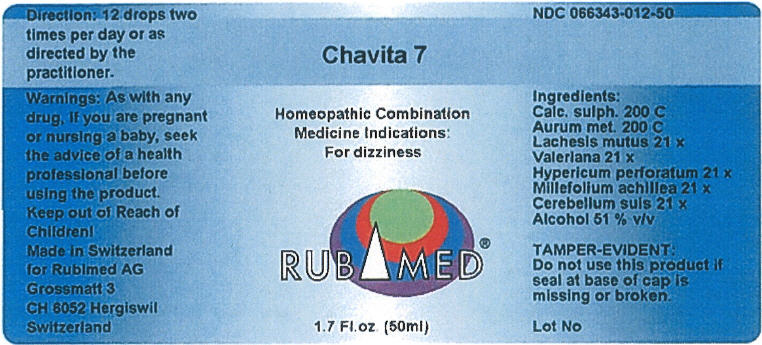 DRUG LABEL: Chavita 7
NDC: 66343-012 | Form: LIQUID
Manufacturer: RUBIMED AG
Category: otc | Type: HUMAN OTC DRUG LABEL
Date: 20150707

ACTIVE INGREDIENTS: CALCIUM SULFATE ANHYDROUS 200 [hp_C]/1 mL; GOLD 200 [hp_C]/1 mL; LACHESIS MUTA VENOM 21 [hp_X]/1 mL; VALERIANA OFFICINALIS WHOLE 21 [hp_X]/1 mL; HYPERICUM PERFORATUM 21 [hp_X]/1 mL; ACHILLEA MILLEFOLIUM 21 [hp_X]/1 mL; SUS SCROFA CEREBRUM 21 [hp_X]/1 mL
INACTIVE INGREDIENTS: Alcohol 0.51 mL/1 mL

Chavita 7

PURPOSE

Homeopathic Combination Medicine Indications: For dizziness

Ingredients

INACTIVE INGREDIENT

Calc. sulph. 200 C
Aurum met. 200 C
Lachesis mutus 21 x
Valeriana 21 x
Hypericum perforatum 21 x
Millefolium achillea 2l x
Cerebrum suis 21 x
Alcohol 51 % v/v

TAMPER-EVIDENT

Do not use this product if seal at base of cap is missing or broken.

Direction

12 drops two times per day or as directed by the practitioner.

Warnings

PREGNANCY OR BREAST FEEDING

As with any drug, if you are pregnant or nursing a baby, seek the advice of a health professional before using the product.

Keep out of Reach of Children!

PRINCIPAL DISPLAY PANEL - 50 ml Bottle Label

Chavita 7

Homeopathic Combination
Medicine Indications:
For dizziness

RUBIMED®

1.7 Fl.oz. (50ml)